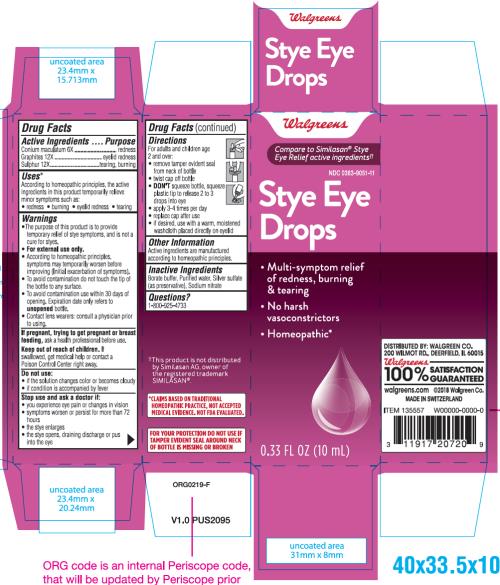 DRUG LABEL: Walgreens Stye Eye Relief
NDC: 0363-9051 | Form: SOLUTION/ DROPS
Manufacturer: Walgreen Company
Category: homeopathic | Type: HUMAN OTC DRUG LABEL
Date: 20211028

ACTIVE INGREDIENTS: CONIUM MACULATUM FLOWERING TOP 6 [hp_C]/10 mL; GRAPHITE 12 [hp_C]/10 mL; SULFUR 12 [hp_C]/10 mL
INACTIVE INGREDIENTS: WATER; SILVER SULFATE; SODIUM NITRATE

Walgreens Stye Eye Drops

Drug Facts

Active Ingredients

Conium maculatum 6X

Graphites 12X

Sulphur 12X

Purpose

redness

eyelid redness

tearing, burning

Uses*

According to homeopathic principles, the active ingredients in this product temporarily relieve minor symptoms such as:

• redness • burning • eyelid redness • tearing

Warnings

•The purpose of this product is to provide temporary relief of stye symptoms, and is not a cure for styes.

• For external use only.

• According to homeopathic principles, symptoms may temporarily worsen before improving (Initial exacerbation of symptoms).

• To avoid contamination do not touch the tip of the bottle to any surface.

• To avoid contamination use within 30 days of opening. Expiration date only refers to unopened bottle.

• Contact wearers: consult a physician prior to using.

If pregnant, trying to get pregnant or breast feeding,

ask a health professional before use.

Keep out of reach of children.

If swallowed, get medical help or contact a Poison Control Center right away.

Do not use:

• if the solution changes color or becomes cloudy

• if condition is accompanied by fever

Stop use and ask a doctor if:

• you experience eye pain or changes in vision

• symptoms worsen or persist for more than 72 hours

• the stye enlarges

• the stye opens, draining discharge or pus into the eye

Directions

For adults and children age

2 and over:

• remove tamper evident seal from neck of bottle

• twist cap off bottle

• DON'T squeeze bottle, squeeze plastic tip to release 2 to 3 drops into eye

• apply 3-4 times per day

• replace cap after use

• if desired, use with a warm, moistened washcloth placed directly on eyelid

Other Information

Active ingredients are manufactured according to homeopathic principles.

Inactive Ingredients

Borate buffer, Purified water, Silver sulfate (as preservative), Sodium nitrate

Questions?

1-800-925-4733

++This product is not distributed by Similasan AG, owner of the registered trademark SIMILASAN®.

*CLAIMS BASED ON TRADITIONAL HOMEOPATHIC PRACTICE, NOT ACCEPTED MEDICAL EVIDENCE. NOT FDA EVALUATED.

FOR YOUR PROTECTION DO NOT USE IF TAMPER EVIDENT SEAL AROUND NECK IS MISSING OR BROKEN

PRINCIPAL DISPLAY PANEL

NDC 0363-9051-11
Stye Eye Relief

Drops
0.33 FL OZ (10 mL)